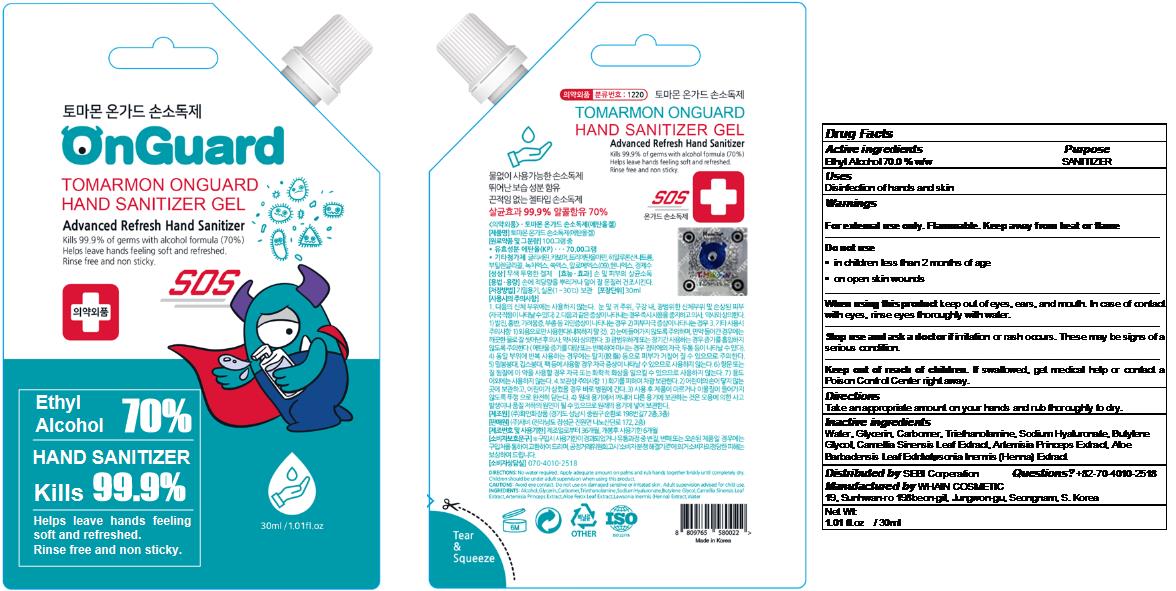 DRUG LABEL: TOMARMON ONGUARD HAND SANITIZER Gel
NDC: 73823-032 | Form: GEL
Manufacturer: WHAIN COSMETIC
Category: otc | Type: HUMAN OTC DRUG LABEL
Date: 20201215

ACTIVE INGREDIENTS: ALCOHOL 21 mL/30 mL
INACTIVE INGREDIENTS: ALOE VERA LEAF; LAWSONIA INERMIS WHOLE; TROLAMINE; GLYCERIN; HYALURONATE SODIUM; BUTYLENE GLYCOL; WATER; ARTEMISIA PRINCEPS LEAF; GREEN TEA LEAF; CARBOMER HOMOPOLYMER, UNSPECIFIED TYPE

[WHAIN COSMETIC] TOMARMON ONGUARD HAND SANITIZER GEL
Blue